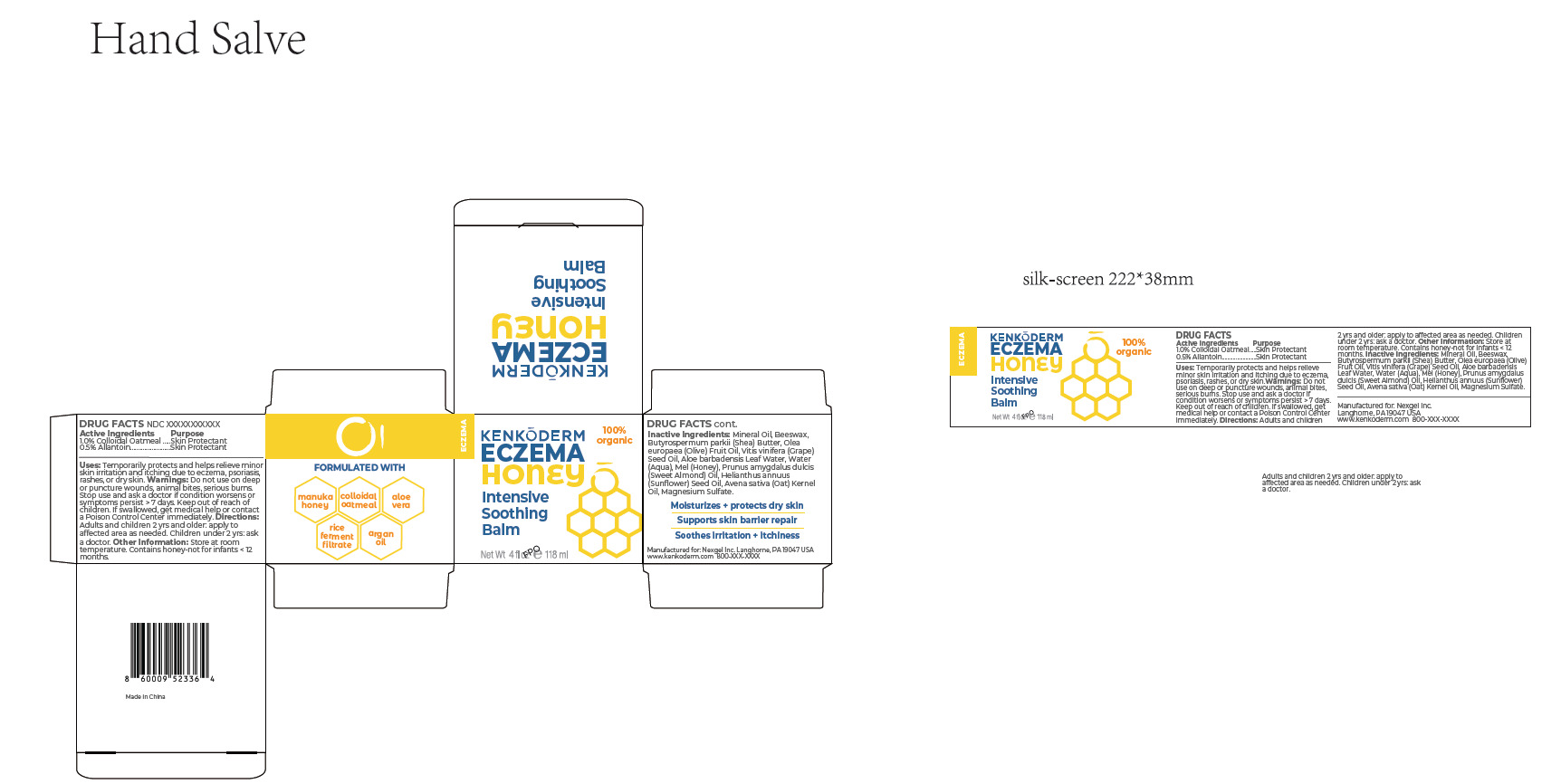 DRUG LABEL: Kenkoderm Eczema Honey Intensive Soothing Balm
NDC: 84148-018 | Form: CREAM
Manufacturer: Guangzhou Ariel Biotech Co., Ltd.
Category: otc | Type: HUMAN OTC DRUG LABEL
Date: 20260114

ACTIVE INGREDIENTS: ALLANTOIN 0.5 g/100 mL; OATMEAL 1 g/100 mL
INACTIVE INGREDIENTS: MINERAL OIL; BEESWAX; BUTYROSPERMUM PARKII (SHEA) BUTTER; OLEA EUROPAEA (OLIVE) FRUIT OIL; VITIS VINIFERA (GRAPE) SEED OIL; ALOE VERA LEAF OIL; WATER; MEL; PRUNUS AMYGDALUS DULCIS (SWEET ALMOND) OIL; HELIANTHUS ANNUUS (SUNFLOWER) SEED OIL; AVENA SATIVA (OAT) KERNEL OIL; MAGNESIUM SULFATE

84148-018
Kenkoderm® Eczema Honey Intensive Soothing Balm

Active Ingredient(s)

1.0% Colloidal Oatmeal

0.5% Allantoin

Purpose

Skin Protectant

Warnings

Do not use on deep or puncture wounds, animal bites, serious burns.
Stop use and ask a doctor if condition worsens or
symptoms persist > 7 days. Keep out of reach of
children. If swallowed, get medical help or contact
a Poison Control Center immediately.

Do not use on deep or puncture wounds,

WHEN USING

If swallowed, get medical help or contact a Poison Control Center immediately.

Stop use and ask a doctor if condition worsens or symptoms persist > 7 days

Keep out of reach of children.

Other information

Store at room temperature. Contains honey-not for infants < 12 months.

Inactive ingredients

Mineral Oil, Beeswax, Butyrospermum parkii (Shea) Butter, Olea europaea (Olive) Fruit Oil, Vitis vinifera (Grape)
Seed Oil, Aloe barbadensis Leaf Water, Water (Aqua), Mel (Honey), Prunus amygdalus dulcis
(Sweet Almond) Oil, Helianthus annuus (Sunflower) Seed Oil, Avena sativa (Oat) Kernel
Oil, Magnesium Sulfate.

Directions

Adults and children 2 yrs and older: apply to
affected area as needed. Children under 2 yrs: ask
a doctor.

Uses

Temporarily protects and helps relieve minor
skin irritation and itching due to eczema, psoriasis,
rashes, or dry skin.